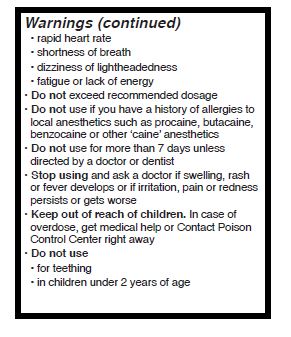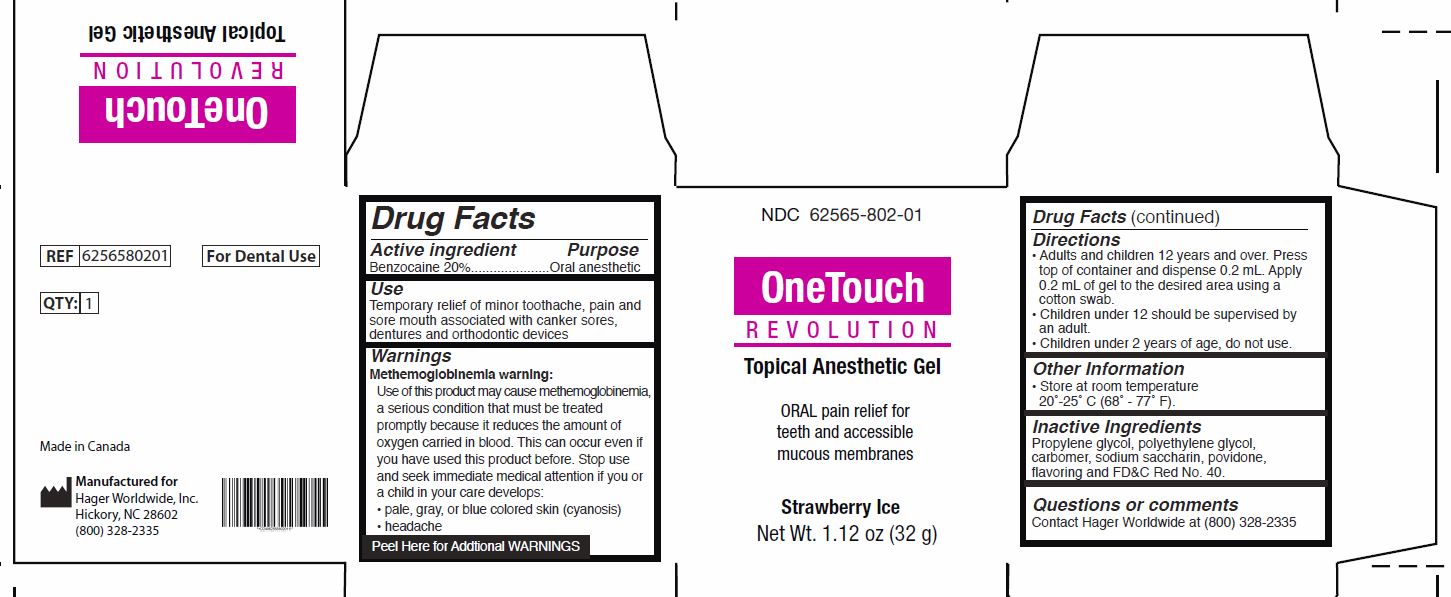 DRUG LABEL: OneTouch Revolution
NDC: 62565-802 | Form: GEL
Manufacturer: HAGER WORLDWIDE, INC.
Category: otc | Type: HUMAN OTC DRUG LABEL
Date: 20180715

ACTIVE INGREDIENTS: Benzocaine 200 mg/1 g
INACTIVE INGREDIENTS: PROPYLENE GLYCOL; POLYETHYLENE GLYCOL, UNSPECIFIED; CARBOXYPOLYMETHYLENE; SACCHARIN SODIUM; POVIDONE, UNSPECIFIED; FD&C RED NO. 40

OneTouch Revolution Topical Anesthetic Gel Strawberry Ice Flavor

Active ingridients (in each gram)

Benzocaine 20%

Purpose

Oral Anesthetic

Use

Temporary relief of minor toothache, pain and sore mouth associated with canker sores, dentures and orthodontic devices

Warnings

Methemoglobinemia warning:

Use of this product may cause methemoglobinemia, a rare but serious condition that must be treated promptly because it reduces the amount of oxygen carried in blood. This can occur even if you have used this product before. Stop use and seek immediate medical attention if they or a child in your care develops:

- pale, gray, or blue colored skin (cyanosis)
- headache
- rapid heart rate
- shortness of breath
- dizziness or lightheadedness
- fatigue or lack of energy

Do not exceed reccommended dosage

Do not use if you have a history of allergies to local anesthetics such as procaine, butacaine, benzocaine or other ‘caine’ anesthetics

Do not use for more than 7 days unless directed by a doctor or dentist

STOP USE

Stop using and ask a doctor if swelling, rash or fever develops or if irritation, pain or redness persists of gets worse

Do not exceed recommended dosage.

Keep out of reach of children. In case of overdose, get medical help or Contact Poison Control Center right away

Do not use

- for teething
- in children under 2 years of age

Directions

Adults and children 12 years and over. Press top of container and dispense 0.2 mL. Apply 0.2 mL of gel to the desired area using a cotton swab.

Children under 12 should be supervised by an adult.

Children under 2 years of age, consult a doctor.

Other information

Store at room temperature
20˚-25˚ C (68˚ - 77˚ F).

Protect from freezing.

Inactive ingredients

Propylene glycol, polyethylene glycol, carbomer, sodium saccharin, povidone, flavoring and FD&C Red No. 40.

Questions or comments

Contact Hager Worldwide at (800) 328-2335

PRINCIPAL DISPLAY PANEL - Jar Label

NDC 62565-802-01
OneTouch
Revolution

Topical Anesthetic Gel

OneTouch Revolution is indicated for anesthesia of accessible mucous membrane.

Strawberry Ice

Net Wt. 1.12 oz (32 g)